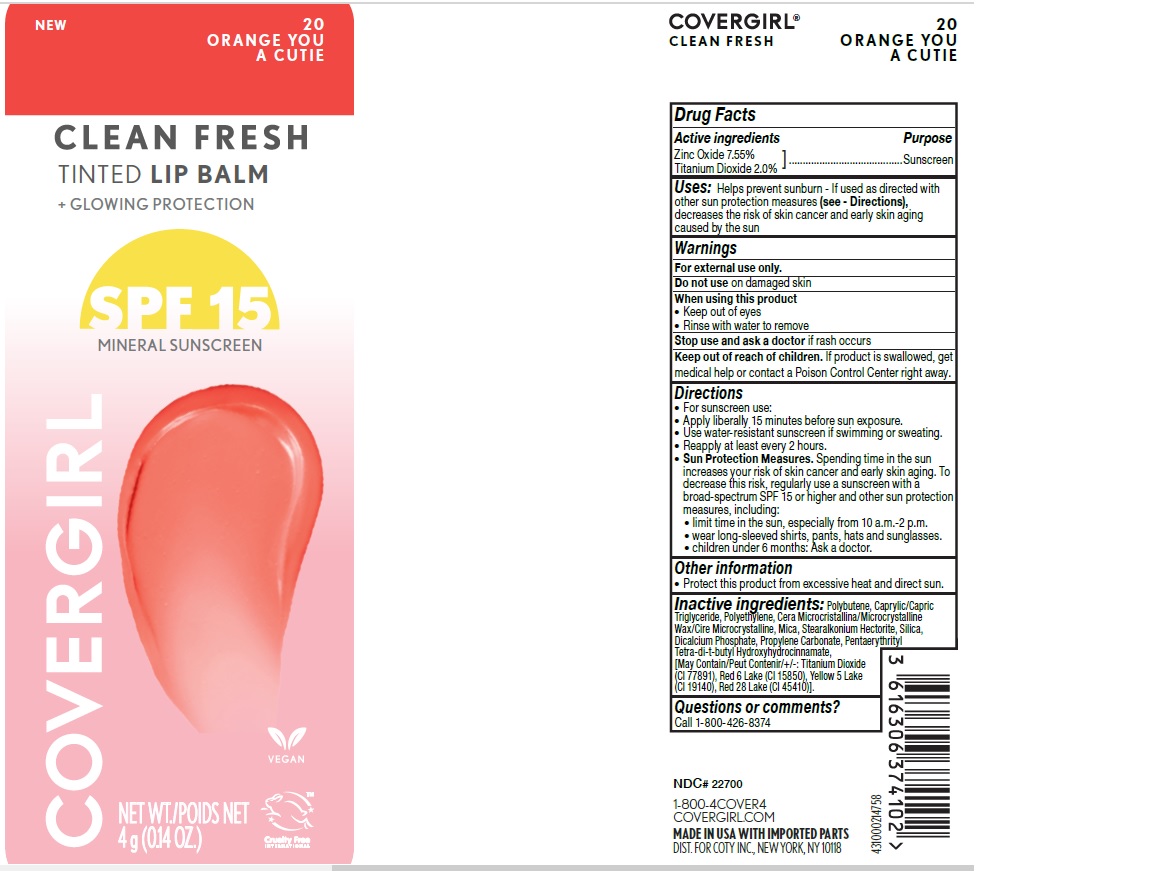 DRUG LABEL: Covergirl Clean Fresh Tinted Lip Balm Glowing Protection SPF 15 Mineral Sunscreen - All shades
NDC: 22700-250 | Form: LIPSTICK
Manufacturer: Noxell
Category: otc | Type: HUMAN OTC DRUG LABEL
Date: 20251217

ACTIVE INGREDIENTS: ZINC OXIDE 75.5 mg/1 mL; TITANIUM DIOXIDE 20 mg/1 mL
INACTIVE INGREDIENTS: FD&C YELLOW NO. 5 ALUMINUM LAKE; FERRIC OXIDE RED; D&C RED NO. 6 BARIUM LAKE; PROPYLENE CARBONATE; D&C RED NO. 28; POLYETHYLENE; STEARALKONIUM HECTORITE; SILICON DIOXIDE; PENTAERYTHRITYL TETRA-DI-T-BUTYL HYDROXYHYDROCINNAMATE; MICROCRYSTALLINE WAX; POLYBUTENE (1400 MW); CAPRYLIC/CAPRIC TRIGLYCERIDE; MICA; DICALCIUM PHOSPHATE; D&C RED NO. 7

Active Ingredients

Zinc Oxide 7.55%

Titanium Dioxide 2%

Purpose

Sunscreen

Uses

Helps prevent sunburn - If used as directed with other sun protection measures (See - Directions), decreases the risk of skin cancer and early skin aging caused by the sun

Warnings

For external use only.

Do not use

on damaged skin

When using this product

- Keep out of eyes
- Rinse with water to remove

Stop use and ask a doctor

if rash occurs

Keep out of reach of children.

If product is swallowed, get medical help or contact a Poison Control Center right away.

Directions

- For sunscreen use:
- Apply liberally 15 minutes before sun exposure.
- Use water-resistant sunscreen if swimming or sweating.
- Reapply at least every 2 hours.
- Sun Protection Measures. Spending time in the sun increases your risk of skin cancer and early skin aging. To decrease this risk, regularly use a sunscreen with a broad-spectrum SPF 15 or higher and other sun protection measure, including:
- limit time in the sun, especially from 10 a.m - 2 p.m.
- wear long-sleeved shirts, pants, hats and sunglassess.
- children under 6 months: Ask a doctor.

Other information

- Protect this product from excessive heat and direct sun.

Inactive ingredients

You Make Me Blush-

Polybutene, Caprylic/Capric Triglyceride, Polyethylene, Cera Microcristallina/Microcrystalline Wax/Cire Microcrystalline, Mica, Stearalkonium Hectorite, Silica, Propylene Carbonate, Pentaerythrityl Tetra-di-t-butyl Hydroxyhydrocinnamate, Dicalcium Phosphate, [May Contain/Peut Contenir/+/-: Titanium Dioxide (CI 77891), Yellow 5 Lake (CI 19140), Red 28 Lake (CI 45410), Iron Oxides (CI 77491, CI 77492, CI 77499), Red 7 Lake (CI 15850)].

Orange You A Cutie-

Polybutene, Caprylic/Capric Triglyceride, Polyethylene, Cera Microcristallina/Microcrystalline Wax/Cire Microcrystalline, Mica, Stearalkonium Hectorite, Silica, Dicalcium Phosphate, Propylene Carbonate, Pentaerythrityl Tetra-di-t-butyl Hydroxyhydrocinnamate,
[May Contain/Peut Contenir/+/-: Titanium Dioxide (CI 77891), Red 6 Lake (CI 15850), Yellow 5 Lake (CI 19140), Red 28 Lake (CI 45410)].

Questions or Comments?

Call 1-800-426-8374